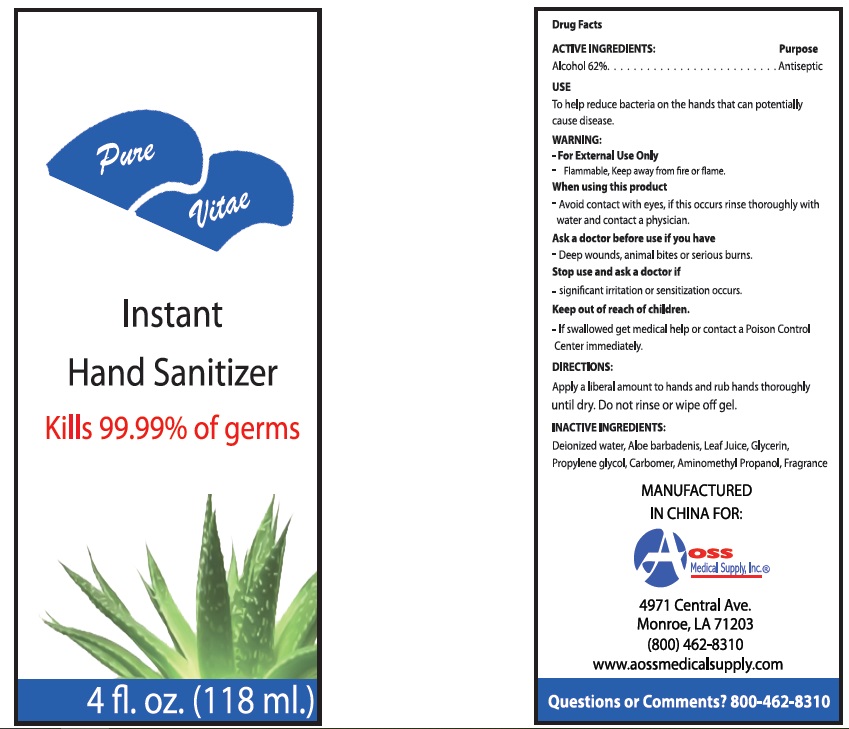 DRUG LABEL: INSTANT HAND SANITIZER
NDC: 53152-2002 | Form: GEL
Manufacturer: AOSS Medical Supply, Inc.
Category: otc | Type: HUMAN OTC DRUG LABEL
Date: 20180604

ACTIVE INGREDIENTS: ALCOHOL 62 mL/100 mL
INACTIVE INGREDIENTS: WATER; ALOE VERA LEAF; GLYCERIN; PROPYLENE GLYCOL; CARBOMER HOMOPOLYMER TYPE C (ALLYL PENTAERYTHRITOL CROSSLINKED); AMINOMETHYLPROPANOL

Active Ingredients:
Ethyl Alcohol 62%

Purpose

Antiseptic

Warning
For External Use Only.
Flammable, Keep away from fire or flame.

Stop use and ask a doctor if
significant irritation or sensitization occurs.

Keep out of reach of children.

If swallowed, get medical help or contact a Poison Control Center immediately.

DIRECTIONS:
Apply a liberal amount to hands and rub hands thoroughly until dry. Do not rinse or wipe off gel.

INACTIVE INGREDIENTS:
Deionized water, Aloe barbadenis, Leaf Juice, Glycerin,
Propylene glycol, Carbomer, Aminomethyl Propanol, Fragrance

Ask a doctor before use if you have
Deep wounds, animal bites or serious burns.

Uses

To help reduce bacteria on the hands that can potentially cause disease.

When using this product
Avoid contact with eyes, if this occurs rinse thoroughly with water and contact a physician.